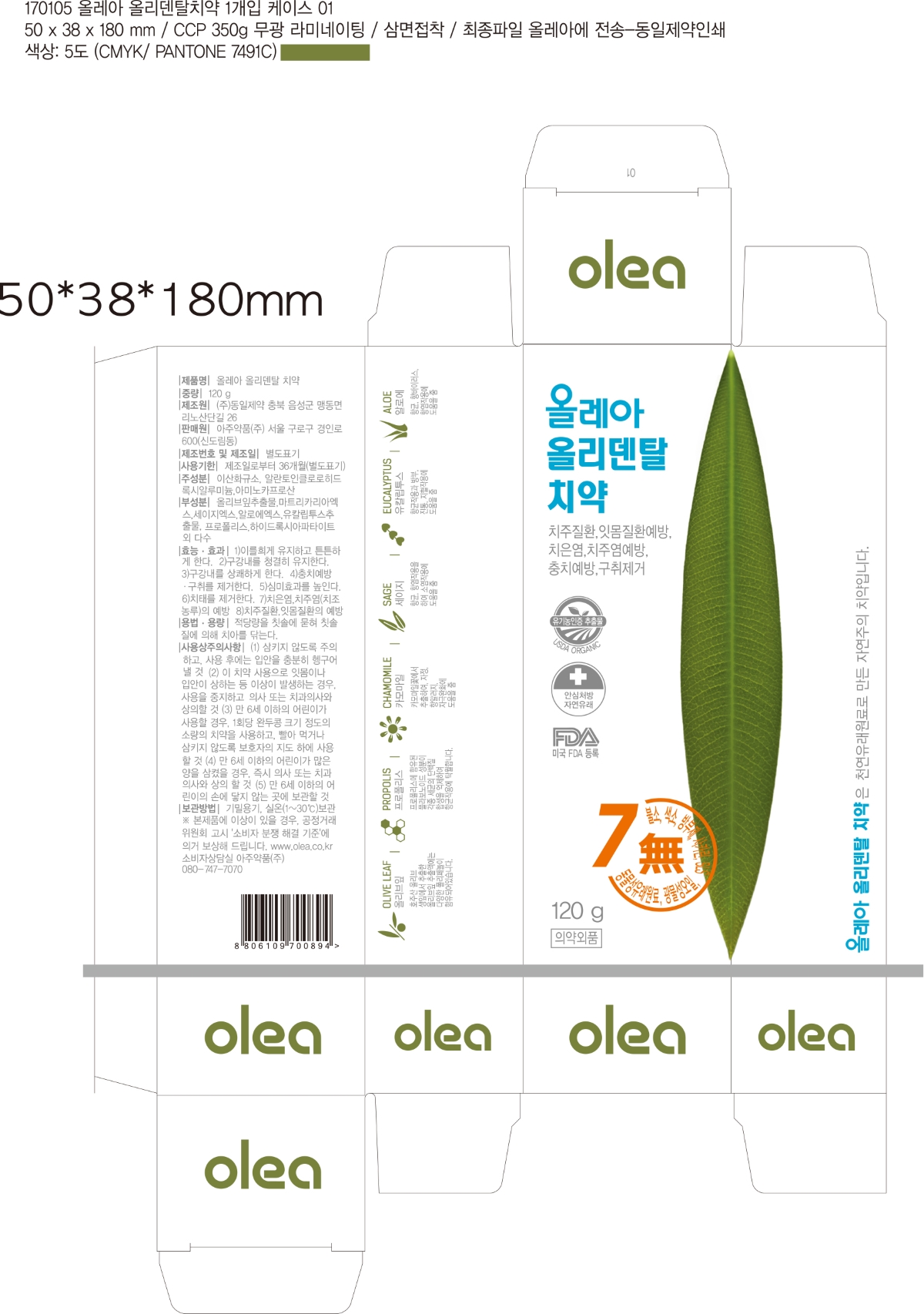 DRUG LABEL: Olea Olidental
NDC: 70417-002 | Form: PASTE
Manufacturer: AJU PHARM CO., LTD.
Category: otc | Type: HUMAN OTC DRUG LABEL
Date: 20170121

ACTIVE INGREDIENTS: SILICON DIOXIDE 170 mg/1 g
INACTIVE INGREDIENTS: ALCLOXA; AMINOCAPROIC ACID; CHAMOMILE; EUCALYPTUS GLOBULUS LEAF; CLARY SAGE; ALOE; CITRUS PARADISI SEED; PROPOLIS WAX; GLYCERIN; XANTHAN GUM; XYLITOL; GLUCOSYL STEVIOL; OLEA EUROPAEA LEAF; TRIBASIC CALCIUM PHOSPHATE; SODIUM COCOYL GLUTAMATE

Drug Facts

ACTIVE INGREDIENT

Silicon Dioxide 17%

PURPOSE

Dental Care

INDICATIONS AND USAGE

To improve dental health and bad breath

DOSAGE AND ADMINISTRATION

Adults and children 2 years of age and older brush teeth thoroughly, preferably after each meal or at least twice a day, or as directed by a dentist or physician

Children 2 to 6 years use only a pea sized amount and supervise child's brushing and rinsing (to minimize swallowing)

Children under 2 years ask a dentist or physician

WARNINGS

Keep out of the reach of children under 6 years of age. If more than used for brushing is accidentally swallowed, get medical help or contact a Poison Control Center right away

KEEP OUT OF REACH OF CHILDREN

Keep out of the reach of children under 6 years of age.

INACTIVE INGREDIENT

Aluminium Chlorohydroxy Allantoinate
Aminocaproic Acid
Chamomile Extract
Eucalyptus Extract
Sage Extract
Aloe Extract
Grapefruit Seed Extract
Propolis Powder
D-Sorbitol Solution
Concentrated Glycerin
Xantangum
Xylitol
Glucosyl Stevia
Olive Leaf Extract
Hydroxyapatite
Sodium Cocoyl Glutamate
Mint Flavor
Begamot Flavor
Solvent